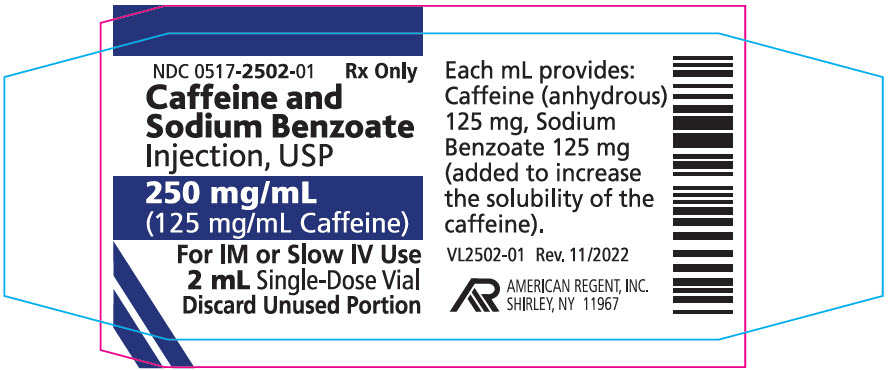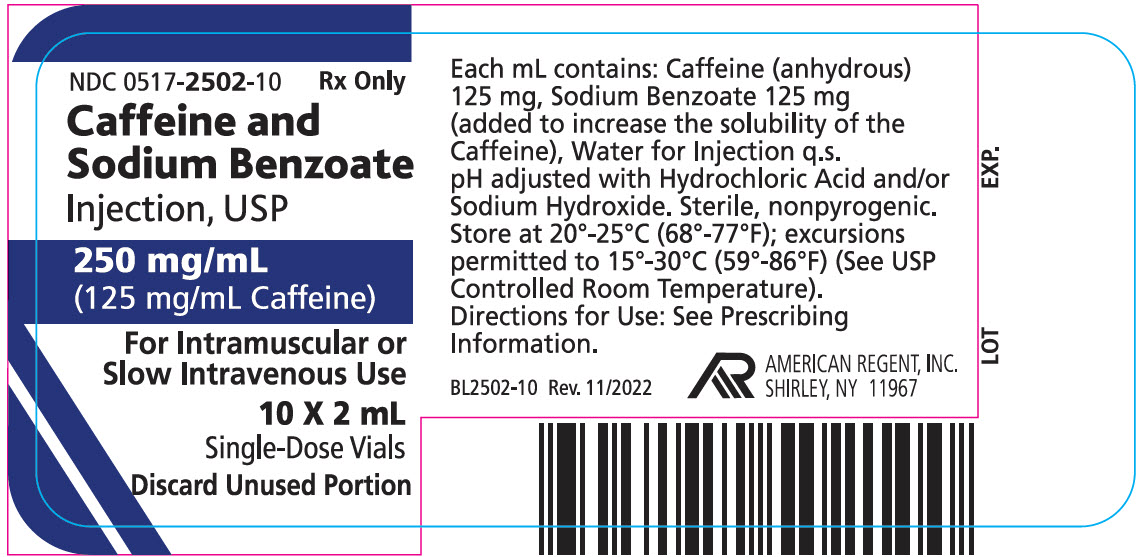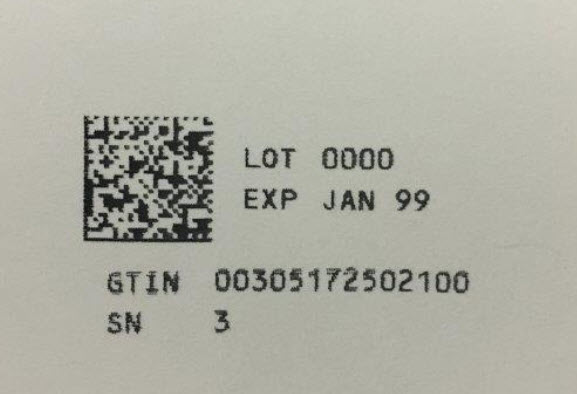 DRUG LABEL: Caffeine and Sodium Benzoate
NDC: 0517-2502 | Form: INJECTION, SOLUTION
Manufacturer: American Regent, Inc.
Category: prescription | Type: HUMAN PRESCRIPTION DRUG LABEL
Date: 20191206

ACTIVE INGREDIENTS: CAFFEINE 125 mg/1 mL
INACTIVE INGREDIENTS: SODIUM BENZOATE 125 mg/1 mL; HYDROCHLORIC ACID; SODIUM HYDROXIDE; WATER

CAFFEINE AND SODIUM BENZOATE INJECTION, USP

Rx Only

DESCRIPTION

Caffeine and Sodium Benzoate Injection, USP is a clear, sterile, nonpyrogenic, solution of Caffeine Alkaloid.

Each mL contains: Caffeine (anhydrous) 125 mg; Sodium Benzoate (added to increase the solubility of Caffeine) 125 mg; Water for Injection, USP q.s. pH (range 6.5 to 8.5) adjusted with Hydrochloric Acid and/or Sodium Hydroxide. For intramuscular or slow intravenous administration only.

CLINICAL PHARMACOLOGY

Caffeine is pharmacologically similar to the other xanthine drugs, such as theobromine and theophylline; however, these three agents differ in the intensity of their actions on various structures. Caffeine's CNS and skeletal muscle effects are greater than those of the other xanthines. In all other areas, theophylline has greater activity than caffeine, although some studies report that caffeine has greater diuretic effect than theobromine. The increased levels of intracellular cyclic-AMP mediate most of caffeine's pharmacologic actions. Caffeine competitively inhibits phosphodiesterase, the enzyme that degrades cyclic 3'- 5' adenosine monophosphate. Caffeine stimulates all levels of the CNS. Caffeine's cortical effects are milder and of shorter duration than those of the amphetamines. In slightly larger doses, caffeine stimulates medullary vagal, vasomotor and respiratory centers, promoting bradycardia, vasoconstriction, and increased respiratory rate.

Caffeine produces a positive inotropic effect of the myocardium and a positive chronotropic effect at the sinoatrial node, causing transient increases in heart rate, force of contraction, cardiac output and heart work. In doses greater than 250 mg, the centrally mediated vagal effects of caffeine may be masked by increased sinus rates; tachycardia, extrasystoles, or other major ventricular arrhythmias may result.

Caffeine constricts cerebral vasculature. In contrast, the drug directly dilates peripheral blood vessels, decreasing peripheral vascular resistance. The effect of this decrease in peripheral vascular resistance (and possibly that of vagal cardiac stimulation) on blood pressure is offset by increased cardiac output (and possibly stimulation of the medullary vasomotor area). The overall effect of caffeine on heart rate and blood pressure depends on whether CNS or peripheral effects predominate. Therapeutic doses of caffeine increase blood pressure only slightly.

Caffeine stimulates voluntary skeletal muscle, increasing the force of contraction and decreasing muscular fatigue. The drug also stimulates gastric acid secretion from parietal cells. Caffeine increases renal blood flow and glomerular filtration rate and decreases proximal tubular reabsorption of sodium and water, resulting in mild diuresis.

Caffeine stimulates glycogenolysis and lipolysis, but increase in blood glucose and in plasma lipids are insignificant in normal patients. Tolerance may develop to the diuretic, cardiovascular, and CNS effects of caffeine.

Pharmacokinetics

Caffeine is rapidly distributed throughout the body tissues, readily crossing the placenta and blood-brain barrier. Approximately 17% of the drug is bound to plasma proteins. Caffeine has approximately a half-life (T ½) of 3-4 hours in adults. In adults, the drug is rapidly metabolized in the liver to 1-methyluric acid, 1-methylxanthine and 7-methylxanthine. Caffeine and its metabolites are excreted primarily by the kidneys.

INDICATIONS AND USAGE

Caffeine and Sodium Benzoate Injection has been used in conjunction with supportive measure to treat respiratory depression associated with overdosage with CNS depressant drugs (e.g., narcotic analgesics, alcohol). However, because of questionable benefit and transient action, most authorities believe caffeine and other analeptics should not be used in these conditions and recommend other supportive therapy.

CONTRAINDICATIONS

None known.

PRECAUTIONS

Large doses of caffeine may produce headache, excitement, agitation, a condition resembling anxiety neurosis, scintillating scotoma, hyperesthesia, tinnitus, muscle tremors or twitches, diuresis, tachycardia, extrasystoles, and other cardiac arrhythmias. Further CNS depression may occur when already depressed patients are too vigorously treated with Caffeine and Sodium Benzoate Injection.

Caffeine and other xanthines may enhance the cardiac inotropic effects of ß-adrenergic stimulating agents. Caffeine has also been reported to increase its own metabolism and that of other drugs, including phenobarbital and aspirin. Caffeine produces false-positive elevations of serum urate as measured by the Bittner method. The drug also produces slight increases in urine levels of vanilamandelic acid (VMA), catecholamines, and 5-hydrocyindoleacetic acid. Because high urine levels of VMA or catecholamines may result in false-positive diagnosis of pheochromocytoma or neuroblastoma, caffeine intake should be avoided during tests for these disorders.

Pregnancy

Teratogenic Effects

Pregnancy Category C. Animal reproduction studies have not been conducted with Caffeine and Sodium Benzoate Injection. It is also not known whether Caffeine and Sodium Benzoate Injection can cause fetal harm when administered to a pregnant woman or can affect reproduction capacity. Caffeine and Sodium Benzoate Injection should be given to a pregnant woman only if clearly needed.

OVERDOSAGE

Acute toxicity involving caffeine has been reported rarely. Mild delirium, insomnia, diuresis, dehydration, and fever commonly occur with overdosage. More serious symptoms of overdosage include cardiac arrhythmias and clonic-tonic convulsions. In adults, IV doses of 57 mg/kg of body weight and oral doses of 18.50 grams have been fatal. In one 5-year-old patient, death occurred following oral ingestion of approximately 3 grams of caffeine. Convulsions may be treated with IV administration of diazepam or a barbiturate such as pentobarbital sodium.

DOSAGE AND ADMINISTRATION

Caffeine and Sodium Benzoate Injection may be administered by intramuscular or slow intravenous injection.

Some clinicians suggest that when used as a mild CNS stimulant to overcome fatigue, oral doses of 100-200 mg of anhydrous caffeine are required. One manufacturer recommends that citrated caffeine be administered orally in dosages of 65-325 mg (about 32-162 mg of anhydrous caffeine) 3 times daily. Another manufacturer recommends an oral dosage of 250 mg of anhydrous caffeine in an extended-release formulation once daily, but warns that the drug should not be administered less than 6 hours before retiring.

Analeptic use of caffeine is strongly discouraged by most clinicians. However, the manufacturer of Caffeine and Sodium Benzoate Injection recommends intramuscular, or in emergency respiratory failure, intravenous injection of 500 mg of the drug (about 250 mg of anhydrous caffeine) or a maximum single dose of 1 gram (about 500 mg of anhydrous caffeine) for the treatment of respiratory depression associated with overdosage of CNS depressants, including narcotic analgesics and alcohol, and with electric shock.

The usual dose is 0.5 g (7 ½ grains) as frequently as directed by the physician. The maximum safe dose is 0.5 g and the total dose in 24 hours should rarely exceed 2.5 g.

Parenteral drug products should be inspected visually for particulate matter prior to administration whenever solution and container permit.

HOW SUPPLIED

Caffeine and Sodium Benzoate Injection, USP 250 mg/mL

NDC 0517-2502-10 2 mL Single Dose Vials Packed in boxes of 10.

Store at 20°-25°C (68°-77°F); excursions permitted to 15°-30"C (59°-86°F) (See USP Controlled Room Temperature).

AMERICAN REGENT, INC.
SHIRLEY, NY 11967

IN2502

Rev. 11/05

PACKAGE LABEL.PRINCIPAL DISPLAY PANEL

Container Label
NDC 0517-2502-01
Rx Only

Caffeine and Sodium Benzoate Injection, USP
250 mg/mL (125 mg/mL Caffeine)
For IM or Slow IV Use

2 mL Single-Dose Vial

Discard Unused Portion

Carton Labeling

NDC 0517-2502-10
Rx Only

Caffeine and Sodium Benzoate Injection, USP

250 mg/mL (125 mg/mL Caffeine)

For Intramuscular or Slow Intravenous Use

10 X 2 mL Single-Dose Vials

Discard Unused Portion